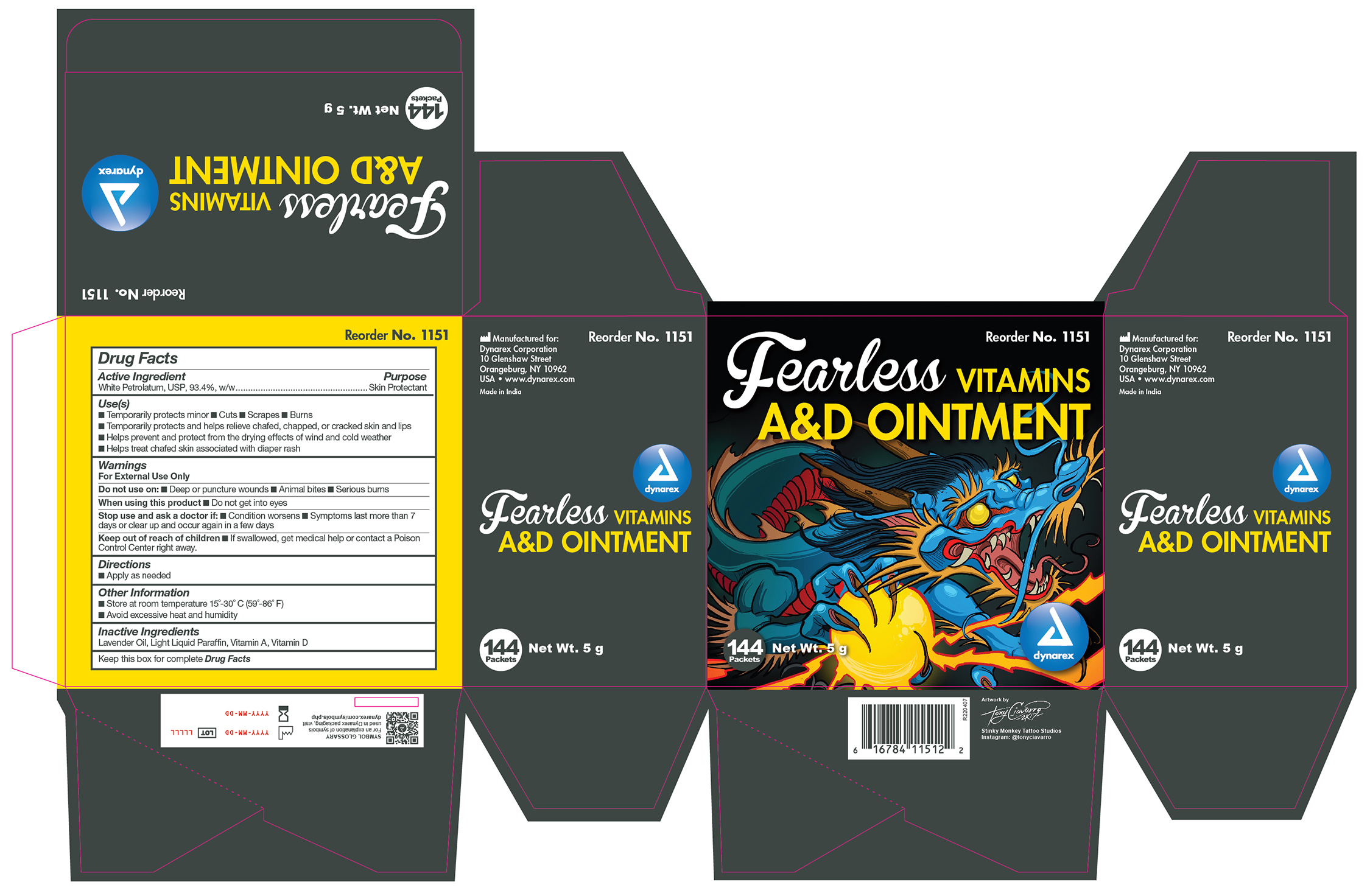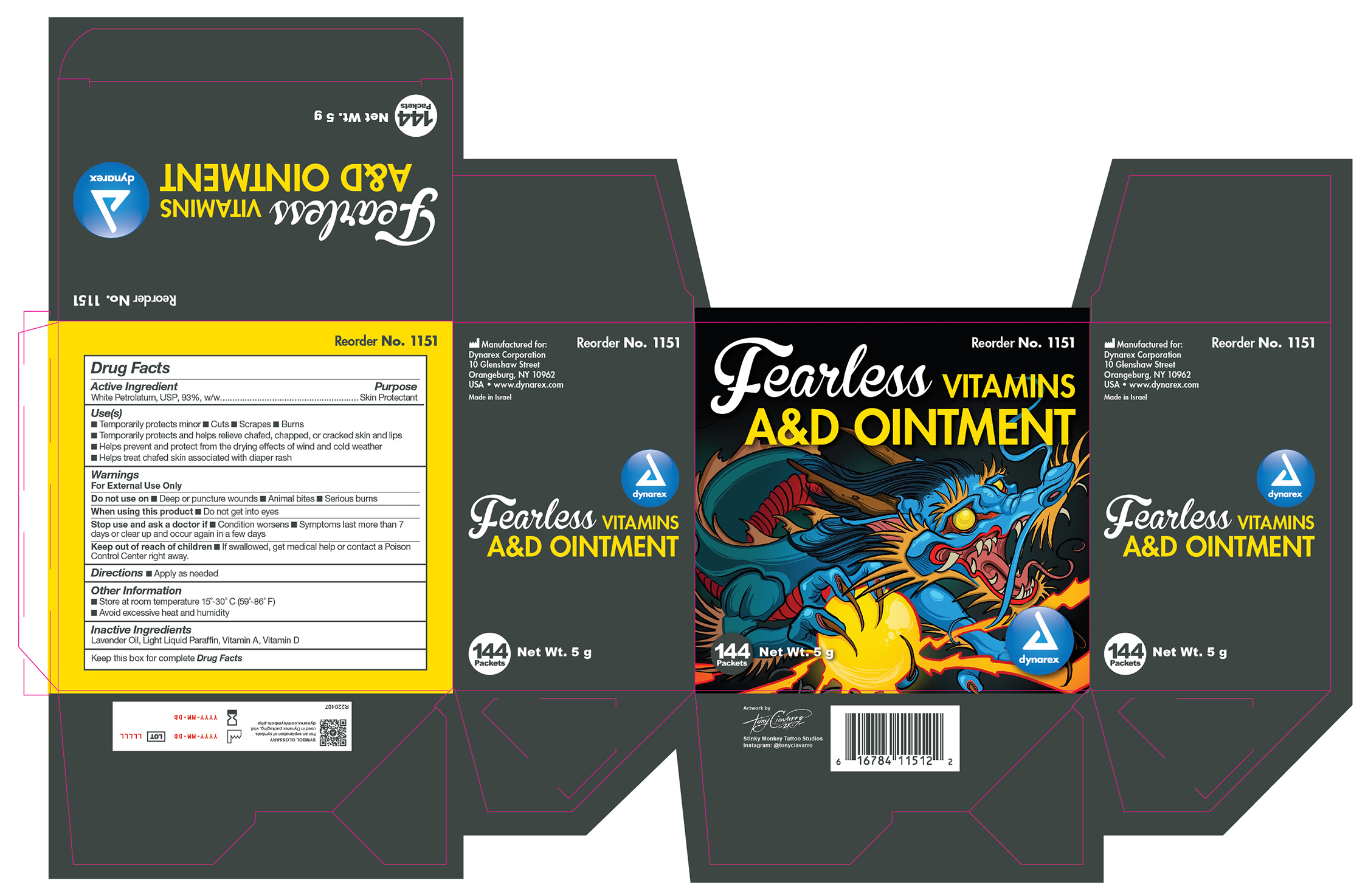 DRUG LABEL: Vitamins A and D Without Lanolin
NDC: 67777-006 | Form: OINTMENT
Manufacturer: Dynarex Corporation
Category: otc | Type: HUMAN OTC DRUG LABEL
Date: 20241120

ACTIVE INGREDIENTS: PETROLATUM 93 g/100 g
INACTIVE INGREDIENTS: LAVENDER OIL; VITAMIN A; LIGHT MINERAL OIL; VITAMIN D

1151 Vitamins A&D Ointment without Lanolin NDC 67777-006-10

Active Ingredient

White Petrolatum, USP, 93%

Purpose

Skin Protectant

Uses

- Temporarily protects minor cuts, scrapes,burns
- Temporarily protects and helps relieve chafed, chapped, or cracked skin and lips
- Helps prevent and protect from the drying effects of wind and cold weather

Warning

For external Use Only

Do not use on

- Deep or puncture wounds
- animal bites
- serious burns

When using this product

do not get into eyes

Stop use and ask a doctor if

- condition worsens
- symptoms last more than 7 days or clear up and occur again in a few days

KEEP OUT OF REACH OF CHILDREN

If swallowed, get medical help or contact a Poison Control Center right away.

Directions

Apply as needed

Other Information

- Store at controlled room temperature 15°-30° C (59°-86° F)
- Avoid excessive heat and humidity
- Tamper evident. Do not use of packet is torn, cut or opened

Inactive Ingredients

- Lavender Oil
- Light Liquid Paraffin
- Vitamin A
- Vitamin D

Label

1151 Label

Label

1151